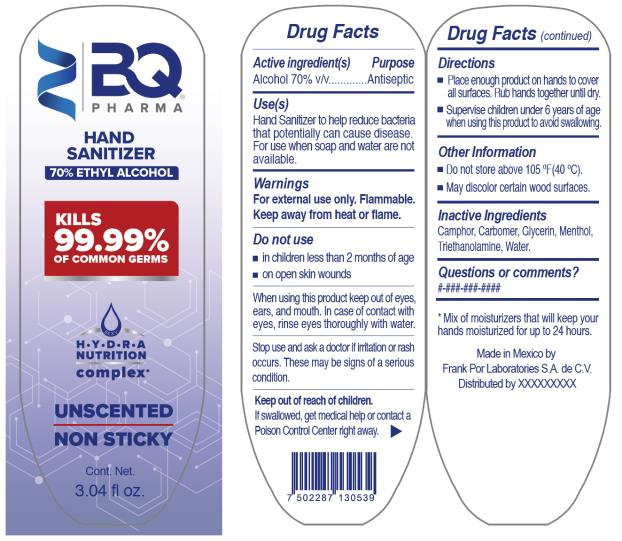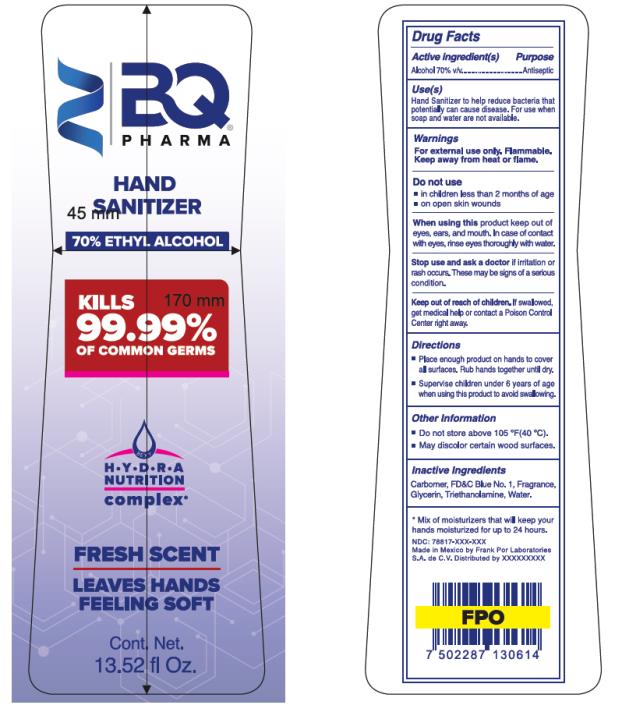 DRUG LABEL: BQ Pharma Hand Sanitizer
NDC: 78817-001 | Form: GEL
Manufacturer: Frank por Laboratories, S.A. de C.V.
Category: otc | Type: HUMAN OTC DRUG LABEL
Date: 20200825

ACTIVE INGREDIENTS: ALCOHOL .70 mL/1 mL
INACTIVE INGREDIENTS: CARBOMER HOMOPOLYMER, UNSPECIFIED TYPE; CAMPHOR (SYNTHETIC); GLYCERIN; MENTHOL; TROLAMINE; WATER

BQ Pharma Hand Sanitizer 70 Percent

DRUG FACTS

Active Ingredient(s)

Alcohol 70% v/v

Purpose

Antiseptic

Use(s)

Hand Sanitizer to help reduce bacteria that potentially can cause disease. For use when soap and water are not available.

Warnings

For external use only. Flammable. Keep away from jeat or flame.

Do not use

- In children less than 2 months of age
- On open skin wounds

When using this product

keep out of eyes, ears and mouth. I case of contact with eyes, rinse eyes thoroughly with water.

Stop use and ask a doctor

if irritation or rash occurs. These may be signs of serious condition.

Keep out of reach of children.

If swallowed, get medical help or contact a Poison Control Center right away.

Directions

- Place enough product on hands to cover all surfaces. Rub hands together until dry.
- Supervise children under 6 years of age when using this product to avoid swallowing.

Other Information

- Do not store above 105ºF (40ºC)
- May discolor certain wood surfaces.

Inactive Ingredients

Camphor, Carbomer, Glycerin, Menthol, Triethanolamine, Water.

Questions or comments?

#-###-###-###

*Mix of mostiurizers that will keep your hands moisturized for up to 24 hours.

Made in Mexico by Frank Por Laboratories S.A. de C.V.

Distributed by XXXXX

DRUG FACTS

Active Ingredient(s)

Alcohol 70% v/v

Purpose

Antiseptic

Use(s)

Hand Sanitizer to help reduce bacteria that potentially can cause disease. For use when soap and water are not available.

Warnings

For external use only. Flammable. Keep away from heat or flame.

Do not use

- In children less than 2 months of age
- On open skin wounds

When using this product

keep out of eyes, ears and mouth. I case of contact with eyes, rinse eyes thoroughly with water.

Stop use and ask a doctor if

irritation or rash occurs. These may be signs of serious condition.

Keep out of reach of children.

If swallowed, get medical help or contact a Poison Control Center right away.

Directions

- Place enough product on hands to cover all surfaces. Rub hands together until dry.
- Supervise children under 6 years of age when using this product to avoid swallowing.

Other Information

- Do not store above 105ºF (40ºC)
- May discolor certain wood surfaces.

Inactive Ingredients

Carbomer, C.I. 42090, Fragrance, Glycerin, Menthol, Triethanolamine, Water.

Questions or comments?

#-###-###-###

*Mix of moisturizers that will keep your hands moisturized for up to 24 hours.

Made in Mexico by Frank Por Laboratories S.A. de C.V.

Distributed by XXXXX

PRINCIPAL DISPLAY PANEL

BQ
Pharma
Hand
Sanitizer
70 % Ethyl Alcohol
3.04 fl oz.

PRINCIPAL DISPLAY PANEL

BQ
PHARMA
HAND
SANITIZER
70 % ETHYL ALCOHOL
13.52 fl Oz.